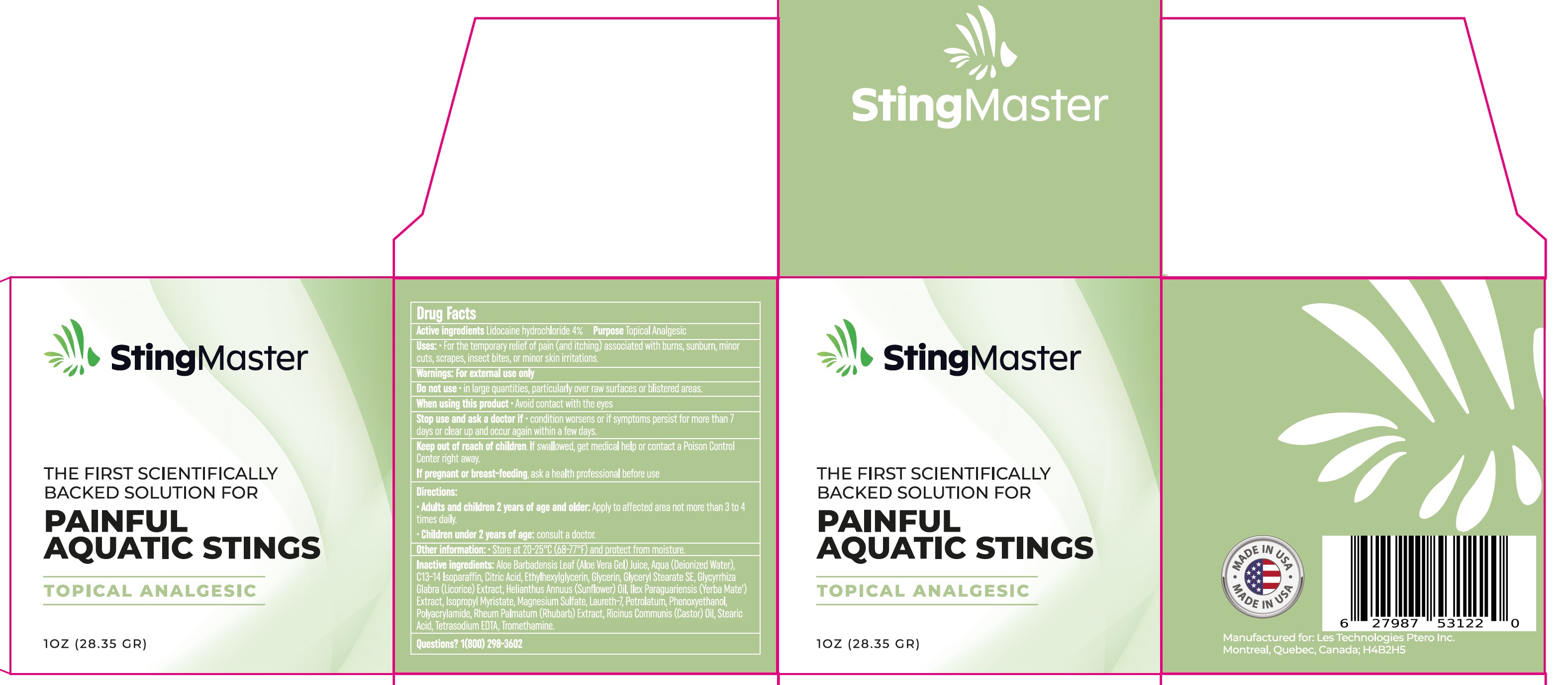 DRUG LABEL: STING MASTER
NDC: 80324-078 | Form: CREAM
Manufacturer: Les Technologies Ptero, Inc
Category: otc | Type: HUMAN OTC DRUG LABEL
Date: 20241105

ACTIVE INGREDIENTS: LIDOCAINE HYDROCHLORIDE 40 mg/1 g
INACTIVE INGREDIENTS: ALOE VERA LEAF; WATER; C13-14 ISOPARAFFIN; CITRIC ACID MONOHYDRATE; ETHYLHEXYLGLYCERIN; GLYCERYL MONOSTEARATE; GLYCYRRHIZA GLABRA; SUNFLOWER OIL; ILEX PARAGUARIENSIS LEAF; ISOPROPYL MYRISTATE; MAGNESIUM SULFATE, UNSPECIFIED FORM; LAURETH-7; PHENOXYETHANOL; RHUBARB; CASTOR OIL; STEARIC ACID; EDETATE SODIUM; TROMETHAMINE

STING MASTER CREAM

Active ingredients

Lidocaine hydrochloride 4%

Purpose

Topical Analgesic

Uses:

- For the temporary relief of pain (and itching) associated with minor burns, sunburn, minor cuts, scrapes, insect bites, or minor skin irritations.

Warnings

For external use only

Do not use

- in large quantities, particularly over raw surfaces or blistered areas.

When using this product

- Avoid contact with the eyes

Stop use and ask a doctor if

- condition worsens, or if symptoms persist for more than 7 days or clear up and occur again within a few days.

Keep out of reach of children.

If swallowed, get medical help or contact a Poison Control Center right away.

If pregnant or breast feeding,

ask a health professional before use.

Directions:

- Apply to affected area not more than 3 to 4 times daily. Adults and children 2 years of age or older:
- Consult a doctor. Children under 2 years of age:

Other information:

- Store at 20-25°C (68-77°F) and protect from moisture.

Other Ingredients

Aloe Barbadensis Leaf (Aloe Vera Gel)Juice, Aqua (Deionized Water,) C13-14 Isoparaffin, Citric Acid, Ethylhexylglycerin, Glyceryl Stearate, Glycyrrhiza Glabra(Licorice)Extract, Helianthus Annuus (Sun flower) Oil, Ilex Paraguariensis (Yerba Mate) Extract, Isopropyl Myristate, Magnesium Sulfate, Laureth-7Petrolatum, Phenoxyethanol, Polyacrylamide, Rheum Palaut m (Rhubarb) Extract, Ricinus Communis (Castor) Oil, Stearic Acid, Tetrasodium EDTA, Tromethamine.

Questions?

1(800) 298-3602